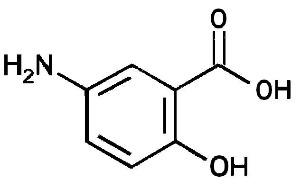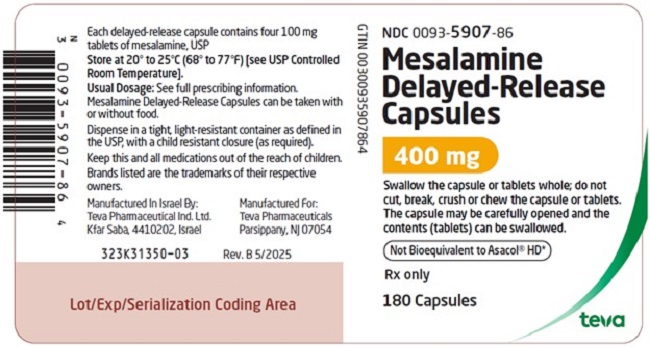 DRUG LABEL: Mesalamine
NDC: 0093-5907 | Form: CAPSULE, DELAYED RELEASE
Manufacturer: Teva Pharmaceuticals USA, Inc.
Category: prescription | Type: HUMAN PRESCRIPTION DRUG LABEL
Date: 20250530

ACTIVE INGREDIENTS: MESALAMINE 400 mg/1 1
INACTIVE INGREDIENTS: SILICON DIOXIDE; DIBUTYL SEBACATE; HYPROMELLOSE, UNSPECIFIED; FERROSOFERRIC OXIDE; FERRIC OXIDE RED; LACTOSE MONOHYDRATE; MAGNESIUM STEARATE; METHACRYLIC ACID - METHYL METHACRYLATE COPOLYMER (1:2); POLYETHYLENE GLYCOL 6000; POTASSIUM HYDROXIDE; POVIDONE K30; PROPYLENE GLYCOL; SHELLAC; SODIUM STARCH GLYCOLATE TYPE A POTATO; AMMONIA; TALC

HIGHLIGHTS OF PRESCRIBING INFORMATION

These highlights do not include all the information needed to use MESALAMINE DELAYED-RELEASE CAPSULES safely and effectively. See full prescribing information for MESALAMINE DELAYED-RELEASE CAPSULES.
MESALAMINE delayed-release capsules, for oral use
Initial U.S. Approval: 1987

1 INDICATIONS AND USAGE

Mesalamine delayed-release capsules are an aminosalicylate indicated for:

- Treatment of mildly to moderately active ulcerative colitis in patients 5 years of age and older. (1.1)
- Maintenance of remission of ulcerative colitis in adults. (1.2)

2 DOSAGE AND ADMINISTRATION

Important Administration Instructions:

- Do not substitute two mesalamine delayed-release 400 mg capsules with one mesalamine delayed-release 800 mg tablet. (2.1)
- Evaluate renal function prior to initiation of mesalamine delayed-release capsules. (2.1, 5.1)
- Take with or without food. (2.1)
- Swallow the capsules whole; do not cut, break, crush or chew. (2.1)
- For patients who are unable to swallow the capsules, the capsules can be opened and the inner tablets swallowed. (2.1)
- Drink an adequate amount of fluids. (2.1, 5.7)

Treatment of Mildly to Moderately Active Ulcerative Colitis:

- Adults: 800 mg (two 400 mg capsules) three times daily for 6 weeks.
- Pediatric Patients 5 years or older: See weight-based dosing table in the full prescribing information; twice daily dosing for 6 weeks. (2.2)

Maintenance of Remission of Ulcerative Colitis:

- Adults: 1.6 grams (four 400 mg capsules) daily, in two to four divided doses. (2.3)

3 DOSAGE FORMS AND STRENGTHS

Delayed-release capsules (containing four 100 mg tablets): 400 mg (3)

4 CONTRAINDICATIONS

Known or suspected hypersensitivity to salicylates or aminosalicylates or to any of the ingredients of mesalamine delayed-release capsules. (4, 5.3)

5 WARNINGS AND PRECAUTIONS

- Renal Impairment: Assess renal function at the beginning of treatment and periodically during treatment. Evaluate the risks and benefits of using mesalamine delayed-release capsules in patients with known renal impairment or taking nephrotoxic drugs; monitor renal function. Discontinue mesalamine delayed-release capsules if renal function deteriorates. (5.1, 7.1, 8.6, 13.2)
- Mesalamine-induced Acute Intolerance Syndrome: Symptoms may be difficult to distinguish from an ulcerative colitis exacerbation; monitor for worsening symptoms while on treatment; discontinue treatment, if acute intolerance syndrome is suspected. (5.2)
- Hypersensitivity Reactions, including myocarditis and pericarditis: Evaluate patients immediately and discontinue mesalamine delayed-release capsules, if a hypersensitivity reaction is suspected. (5.3)
- Hepatic Failure: Evaluate the risks and benefits of using mesalamine delayed-release capsules in patients with known liver impairment. (5.4)
- Severe Cutaneous Adverse Reactions: Discontinue at the first signs or symptoms of severe cutaneous adverse reactions or other signs of hypersensitivity and consider further evaluation. (5.5)
- Photosensitivity: Advise patients with pre-existing skin conditions to avoid sun exposure, wear protective clothing, and use a broad-spectrum sunscreen when outdoors. (5.6)
- Nephrolithiasis: Mesalamine-containing stones undetectable by standard radiography or computed tomography (CT). Ensure adequate fluid intake during treatment. (5.7)
- Iron Content of Mesalamine Delayed-Release Capsules: Consider the iron content of mesalamine delayed-release capsules in patients taking iron supplementation and those at risk of iron overload. (5.8)
- Interference with Laboratory Tests: Use of mesalamine may lead to spuriously elevated test results when measuring urinary normetanephrine by liquid chromatography with electrochemical detection. (5.9)

6 ADVERSE REACTIONS

The most common adverse reactions (≥5%) are:

- Adults: eructation, abdominal pain, constipation, dizziness, rhinitis, back pain, and rash. (6.1)
- Pediatrics: nasopharyngitis, headache, abdominal pain, dizziness, sinusitis, rash, cough and diarrhea. (6.1)

To report SUSPECTED ADVERSE REACTIONS, contact Teva at 1-888-838-2872 or FDA at 1-800-FDA-1088 or www.fda.gov/medwatch.

7 DRUG INTERACTIONS

- Nephrotoxic Agents including NSAIDs: Increased risk of nephrotoxicity; monitor for changes in renal function and mesalamine-related adverse reactions. (7.1)
- Azathioprine or 6-Mercaptopurine: Increased risk of blood disorders; monitor complete blood cell counts and platelet counts. (7.2)

8 USE IN SPECIFIC POPULATIONS

Geriatric Patients: Increased risk of blood dyscrasias; monitor complete blood cell counts and platelet counts. (8.5)

FULL PRESCRIBING INFORMATION

RECENT MAJOR CHANGES

- Warnings and Precautions
  Renal impairment

1 INDICATIONS AND USAGE

1.1 Treatment of Mildly to Moderately Active Ulcerative Colitis

Mesalamine delayed-release capsules are indicated for the treatment of mildly to moderately active ulcerative colitis in patients 5 years of age and older.

1.2 Maintenance of Remission of Ulcerative Colitis

Mesalamine delayed-release capsules are indicated for the maintenance of remission of ulcerative colitis in adults.

2 DOSAGE AND ADMINISTRATION

2.1 Important Administration Instructions

- Do not substitute two mesalamine delayed-release 400 mg capsules with one mesalamine delayed-release 800 mg tablet.
- Evaluate renal function prior to initiation of mesalamine delayed-release capsules.
- Take mesalamine delayed-release capsules with or without food.
- Swallow the capsules whole; do not cut, break, crush or chew the capsules.
- For patients who are unable to swallow the capsules whole, carefully open the capsule(s) and swallow the contents (four 100 mg tablets).
  - Open the number of capsules required to make up a complete dose [see Dosage and Administration (2.2, 2.3)].
  - There are 4 tablets per capsule. Ensure all tablets per capsule are swallowed and no tablets are retained in the mouth.
  - Swallow the tablets whole; do not cut, break, crush or chew the tablets.
- Drink an adequate amount of fluids [see Warnings and Precautions (5.7)].
- Intact, partially intact, and/or tablet shells have been reported in the stool; Instruct patients to contact their healthcare provider if this occurs repeatedly. Protect mesalamine delayed-release capsules from moisture. Close the container tightly and leave any desiccant pouches present in the bottle along with the capsules.

2.2 Dosage for Treatment of Mildly to Moderately Active Ulcerative Colitis

Adults

For adults, the recommended dosage of mesalamine delayed-release capsules is 800 mg (two 400 mg capsules) three times daily (total daily dosage of 2.4 grams) for a duration of 6 weeks [see Clinical Studies (14.1)].

Pediatrics

For pediatric patients 5 years of age and older, the recommended total daily dosage of mesalamine delayed-release capsules is weight-based (up to maximum of 2.4 grams per day) divided into two daily doses for a duration of 6 weeks (see Table 1).

Table 1. Pediatric Dosage by Weight
Weight Group (kg) | Daily Dosage (mg/kg/day) | Maximum Daily Dosage (grams per day) | Morning Dosage | Afternoon Dosage
17 to 32 | 36 to 71 | 1.2 | two 400 mg capsules | one 400 mg capsules
33 to 53 | 37 to 61 | 2 | three 400 mg capsules | two 400 mg capsules
54 to 90 | 27 to 44 | 2.4 | three 400 mg capsules | three 400 mg capsules

2.3 Dosage for Maintenance of Remission of Ulcerative Colitis

The recommended dosage of mesalamine delayed-release capsules in adults is 1.6 grams (four 400 mg capsules) daily in two to four divided doses.

3 DOSAGE FORMS AND STRENGTHS

Mesalamine delayed-release capsules are clear capsules imprinted with “TEVA” and “5907” on both the cap and the body in black ink. Each capsule contains four reddish-brown, film-coated round 100 mg mesalamine tablets.

4 CONTRAINDICATIONS

Mesalamine delayed-release capsules are contraindicated in patients with known or suspected hypersensitivity to salicylates or aminosalicylates or to any of the ingredients of mesalamine delayed-release capsules [see Warnings and Precautions (5.3), Adverse Reactions (6.2), Description (11)].

5 WARNINGS AND PRECAUTIONS

5.1 Renal Impairment

Renal impairment, including minimal change disease, acute and chronic interstitial nephritis, and renal failure, has been reported in patients taking products such as mesalamine delayed-release capsules that contain mesalamine or are converted to mesalamine. In animal studies, the kidney was the principal organ of mesalamine toxicity [see Adverse Reactions (6.2), Nonclinical Toxicology (13.2)].

Evaluate renal function prior to initiation of mesalamine delayed-release capsules and periodically while on therapy. Discontinue mesalamine delayed-release capsules if renal function deteriorates while on therapy.

Evaluate the risks and benefits of using mesalamine delayed-release capsules in patients with known renal impairment or history of renal disease or taking concomitant nephrotoxic drugs [see Drug Interactions (7.1), Use in Specific Populations (8.6)].

5.2 Mesalamine-Induced Acute Intolerance Syndrome

Mesalamine has been associated with an acute intolerance syndrome that may be difficult to distinguish from an exacerbation of ulcerative colitis. Although the exact frequency of occurrence has not been determined, it has occurred in 3% of controlled clinical trials of mesalamine or sulfasalazine. Symptoms include cramping, abdominal pain, bloody diarrhea, and sometimes fever, headache, malaise, pruritus, conjunctivitis and rash. Monitor patients closely for worsening of these symptoms while on treatment. If acute intolerance syndrome is suspected, promptly discontinue treatment with mesalamine delayed-release capsules.

5.3 Hypersensitivity Reactions

Hypersensitivity reactions have been reported in patients taking sulfasalazine. Some patients may have a similar reaction to mesalamine or to other compounds that contain or are converted to mesalamine.

As with sulfasalazine, mesalamine-induced hypersensitivity reactions may present as internal organ involvement, including myocarditis, pericarditis, nephritis, hepatitis, pneumonitis, and hematologic abnormalities. Evaluate patients immediately if signs or symptoms of a hypersensitivity reaction are present. Discontinue mesalamine delayed-release capsules if an alternative etiology for the signs or symptoms cannot be established.

5.4 Hepatic Failure

There have been reports of hepatic failure in patients with pre-existing liver disease who have been administered mesalamine. Evaluate the risk and benefits of using mesalamine delayed-release capsules in patients with known liver impairment.

5.5 Severe Cutaneous Adverse Reactions

Severe cutaneous adverse reactions, including Stevens-Johnson syndrome (SJS) and toxic epidermal necrolysis (TEN), drug reaction with eosinophilia and systemic symptoms (DRESS), and acute generalized exanthematous pustulosis (AGEP) have been reported with the use of mesalamine [see Adverse Reactions (6.2)]. Discontinue mesalamine delayed-release capsules at the first appearance of signs or symptoms of severe cutaneous adverse reactions, or other signs of hypersensitivity and consider further evaluation.

5.6 Photosensitivity

Patients treated with mesalamine or sulfasalazine who have pre-existing skin conditions such as atopic dermatitis and atopic eczema have reported more severe photosensitivity reactions. Advise patients to avoid sun exposure, wear protective clothing, and use a broad-spectrum sunscreen when outdoors.

5.7 Nephrolithiasis

Cases of nephrolithiasis have been reported with the use of mesalamine, including stones of 100% mesalamine content. Mesalamine-containing stones are radiotransparent and undetectable by standard radiography or computed tomography (CT). Ensure adequate fluid intake during treatment with mesalamine delayed-release capsules.

5.8 Iron Content of Mesalamine Delayed-Release Capsules

Mesalamine delayed-release capsules contains iron oxide as a colorant in the coating of the delayed-release capsules. Each 400 mg delayed-release capsule contains 0.589 mg of iron. The total content of iron is 3.54 mg at the maximum recommended daily dosage in adults [see Dosage and Administration (2.2)]. Before prescribing mesalamine delayed-release capsules to patients receiving iron supplementation or those at risk of developing iron overload, consider the combined daily amount of iron from all sources, including mesalamine delayed-release capsules.

5.9 Interference with Laboratory Tests

Use of mesalamine delayed-release capsules may lead to spuriously elevated test results when measuring urinary normetanephrine by liquid chromatography with electrochemical detection because of the similarity in the chromatograms of normetanephrine and the main metabolite of mesalamine, N-acetyl-5-aminosalicylic acid (N-Ac-5-ASA). Consider an alternative, selective assay for normetanephrine.

6 ADVERSE REACTIONS

The most serious adverse reactions seen in mesalamine clinical trials or with other products that contain or are metabolized to mesalamine are:

- Renal Impairment [see Warnings and Precautions (5.1)]
- Mesalamine-Induced Acute Intolerance Syndrome [see Warnings and Precautions (5.2)]
- Hypersensitivity Reactions [see Warnings and Precautions (5.3)]
- Hepatic Failure [see Warnings and Precautions (5.4)]
- Severe Cutaneous Adverse Reactions [see Warnings and Precautions (5.5)]
- Photosensitivity [see Warnings and Precautions (5.6)]
- Nephrolithiasis [see Warnings and Precautions (5.7)]

6.1 Clinical Trials Experience

Because clinical trials are conducted under widely varying conditions, adverse reaction rates observed in the clinical trials of a drug cannot be directly compared to rates in the clinical trials of another drug and may not reflect the rates observed in practice.

The safety of mesalamine has been established based on adequate and well-controlled studies of mesalamine delayed-release tablets. In total, mesalamine delayed-release 400 mg tablets have been evaluated in 2690 patients with ulcerative colitis in controlled and open-label trials. Below is a description of the adverse reactions of mesalamine delayed-release tablets in these adequate and well-controlled studies.

Clinical studies supporting mesalamine delayed-release tablets use for the treatment of mildly to moderately active ulcerative colitis included two 6-week, placebo-controlled, randomized, double-blind studies in adults with mildly to moderately active ulcerative colitis (Studies 1 and 2), and one 6-week, randomized, double-blind, study of 2 dosage levels in children with mildly to moderately active ulcerative colitis (Study 3). Clinical studies supporting the use of mesalamine delayed-release tablets in the maintenance of remission of ulcerative colitis included a 6-month, randomized, double-blind, placebo-controlled, multi-center study (Study 4) and four active-controlled maintenance trials comparing mesalamine delayed-release with sulfasalazine. Mesalamine delayed-release tablets have been evaluated in 427 adults and 107 children with ulcerative colitis in these controlled studies.

Treatment of Mildly to Moderately Active Ulcerative Colitis

Adults

In a 6-week placebo-controlled clinical study (Study 1) involving 105 patients, 53 of whom were randomized to mesalamine delayed-release tablets 2.4 grams per day [see Clinical Studies (14.1)], 4% of the mesalamine delayed release tablets-treated patients in 2.4 grams per day group discontinued therapy because of adverse reactions as compared to 0% of the placebo-treated patients. The average age of patients was 41 years and 49% of patients were male. Adverse reactions leading to withdrawal from mesalamine delayed-release tablets included (each in one patient): diarrhea and colitis flare; dizziness, nausea, joint pain, and headache.

The most common adverse reactions in patients treated with mesalamine delayed release tablets 2.4 grams per day in Study 1 are listed in Table 2 below.

Table 2. Most Common Adverse Reactions Reported in Study 1 for the Treatment of Mild to Moderate Ulcerative Colitis in Adults*
Adverse Reaction | % of Patients with Adverse Reactions
Adverse Reaction | Mesalamine Delayed-Release 2.4 grams per day | Placebo
Adverse Reaction | (n = 53) | (n = 52)
Eructation | 26 | 19
Abdominal pain | 21 | 12
Constipation | 11 | 0
Dizziness | 9 | 8
Rhinitis | 8 | 6
Back pain | 6 | 4
Rash | 6 | 4
Dyspepsia | 4 | 0
Flu syndrome | 4 | 2
* At Least 2% of Patients in the Mesalamine Delayed-Release Tablets Group and at a Rate Greater than Placebo

Pediatric Patients 5 to 17 Years Old

A randomized, double-blind, 6-week study of 2 dosage levels of mesalamine delayed-release 400 mg tablets (Study 3) was conducted in 82 pediatric patients 5 to 17 years of age with mildly to moderately active ulcerative colitis. All patients were divided by body weight category (17 to less than 33 kg, 33 to less than 54 kg, and 54 to 90 kg) and randomly assigned to receive a low dosage (1.2, 2, and 2.4 grams per day for the respective body weight category) or a high dosage (2.0, 3.6, and 4.8 grams per day).

The high dosage regimen is not recommended because it was not found to be more effective than the recommended low dosage regimen [see Dosage and Administration (2.2), Clinical Studies (14.1)].

Duration of exposure to mesalamine among the 82 patients in the study ranged from 12 to 50 days (mean of 40 days in each dosage group). The majority (88%) of patients in each group were treated for more than 5 weeks. Table 3 provides a summary of the specific reported adverse reactions.

Table 3. Adverse Reactions ≥ 5% Reported in Study 3 for the Treatment of Mild to Moderate Ulcerative Colitis in Pediatric Patients*
Adverse Reaction | % of Patients with Adverse Reactions
Adverse Reaction | Low Dosage | High Dosage
Adverse Reaction | (n=41) | (n=41)
Nasopharyngitis | 15 | 12
Headache | 10 | 5
Abdominal pain | 10 | 2
Dizziness | 7 | 2
Sinusitis | 7 | 0
Rash | 5 | 5
Cough | 5 | 0
Diarrhea | 5 | 0
Fatigue | 2 | 10
Pyrexia | 0 | 7
Increased Lipase | 0 | 5
Low Dosage = mesalamine 400 mg delayed-release tablet 1.2 to 2.4 grams/day; High Dosage = mesalamine 400 mg delayed-release tablet 2.0 to 4.8 grams/day. Dosage was dependent on body weight.
Adverse Reactions reported at the 1-week telephone follow-up visit are included.
* At Least 5% of Patients in the low dosage or high dosage group

Twelve percent of the patients in the low dosage group (5 patients) and 2% of the patients in the high dosage group (1 patient) had serious adverse reactions. The serious adverse reactions consisted of sinusitis, adenovirus infection, and pancreatitis in one patient each in the low dosage group. Abdominal pain and decreased body mass index occurred in one patient and bloody diarrhea and sclerosing cholangitis also occurred in one patient in the low dosage group. Anemia and syncope occurred in one patient in the high dosage group.

Five patients were withdrawn from the study due to adverse reactions: 3 (7%) in the low dosage group (1 patient each with adenovirus infection, sclerosing cholangitis, and pancreatitis) and 2 patients (5%) in the high dosage group (1 patient with increased amylase and increased lipase, and 1 patient with upper abdominal pain).

In general, the nature and severity of reactions in the pediatric population was similar to those reported in adult populations of patients with ulcerative colitis.

Maintenance of Remission of Ulcerative Colitis

Clinical studies supporting the use of mesalamine delayed release tablets in the maintenance of remission of ulcerative colitis in adults included a randomized, double-blind, multi-center, placebo-controlled clinical trial of 6 months’ duration in 264 patients (Study 4) [see Clinical Studies (14.2)].

In Study 4, a randomized, double-blind, multi-center, placebo-controlled clinical trial of 6 months’ duration, 87 patients were randomized to receive mesalamine delayed release tablets 1.6 grams per /day compared to 87 patients randomized to placebo. The average age of patients in Study 4 was 42 years and 55% of patients were male. Adverse reactions leading to study withdrawal in patients using mesalamine delayed release tablets included (each in one patient): anxiety, stomatitis and asthenia.

In addition to the adverse reactions listed in Table 2, the following occurred at a frequency of 2% or greater in patients who received mesalamine delayed-release tablets in Study 4: abdominal enlargement, gastroenteritis, gastrointestinal hemorrhage, infection, joint disorder, nervousness, paresthesia, hemorrhoids, tenesmus, urinary frequency and vision abnormalities.

6.2 Postmarketing Experience

The following adverse reactions have been identified during post-approval use of mesalamine delayed-release capsules or other mesalamine-containing products. Because these reactions are reported voluntarily from a population of uncertain size, it is not always possible to reliably estimate their frequency or establish a causal relationship to drug exposure.

Body as a Whole: Neck pain, facial edema, edema, lupus-like syndrome, drug fever.

Cardiovascular: Pericarditis, myocarditis [see Warnings and Precautions (5.3)].

Endocrine: Nephrogenic diabetes insipidus.

Gastrointestinal: Anorexia, pancreatitis, gastritis, increased appetite, cholecystitis, dry mouth, oral ulcers, perforated peptic ulcer, bloody diarrhea.

Hematologic: Agranulocytosis, aplastic anemia, thrombocytopenia, eosinophilia, leukopenia, anemia, lymphadenopathy.

Musculoskeletal: Gout.

Nervous: Depression, somnolence, emotional lability, hyperesthesia, vertigo, confusion, tremor, peripheral neuropathy, transverse myelitis, Guillain-Barré syndrome, intracranial hypertension.

Renal: Renal failure, interstitial nephritis, minimal change disease, nephrolithiasis [see Warnings and Precautions (5.1, 5.7)].

Respiratory/Pulmonary: Eosinophilic pneumonia, interstitial pneumonitis, asthma exacerbation, pleurisy/pleuritis.

Skin: Alopecia, psoriasis, pyoderma gangrenosum, dry skin, erythema nodosum, urticaria, SJS/TEN, DRESS, and AGEP [see Warnings and Precautions (5.5)].

Special Senses: Eye pain, taste perversion, blurred vision, tinnitus.

Urogenital: Dysuria, urinary urgency, hematuria, epididymitis, menorrhagia, reversible oligospermia.

- Urine discoloration occurring ex-vivo caused by contact of mesalamine, including inactive metabolite, with surfaces or water treated with hypochlorite containing bleach

Laboratory Abnormalities: Elevated AST (SGOT) or ALT (SGPT), elevated alkaline phosphatase, elevated GGT, elevated LDH, elevated bilirubin, elevated serum creatinine and BUN.

7 DRUG INTERACTIONS

7.1 Nephrotoxic Agents, Including Non-Steroidal Anti-Inflammatory Drugs

The concurrent use of mesalamine with known nephrotoxic agents, including non-steroidal anti-inflammatory drugs (NSAIDs) may increase the risk of nephrotoxicity. Monitor patients taking nephrotoxic drugs for changes in renal function and mesalamine-related adverse reactions [see Warnings and Precautions (5.1)].

7.2 Azathioprine or 6-Mercaptopurine

The concurrent use of mesalamine with azathioprine or 6-mercaptopurine and/or other drugs known to cause myelotoxicity may increase the risk for blood disorders, bone marrow failure, and associated complications. If concomitant use of mesalamine delayed-release capsules and azathioprine or 6-mercaptopurine cannot be avoided, monitor blood tests, including complete blood cell counts and platelet counts.

7.3 Interference With Urinary Normetanephrine Measurements

Use of mesalamine delayed-release capsules may lead to spuriously elevated test results when measuring urinary normetanephrine by liquid chromatography with electrochemical detection [see Warnings and Precautions (5.9)]. Consider an alternative, selective assay for normetanephrine.

8 USE IN SPECIFIC POPULATIONS

8.1 Pregnancy

Risk Summary

There are no adequate and well controlled studies of mesalamine use in pregnant women. Limited published human data on mesalamine show no increase in the overall rate of congenital malformations. Some data show an increased rate of preterm birth, stillbirth, and low birth weight; however, these adverse pregnancy outcomes are also associated with active inflammatory bowel disease. Furthermore, all pregnancies, regardless of drug exposure, have a background rate of 2% to 4% for major malformations, and 15% to 20% for pregnancy loss. No evidence of fetal harm was observed in animal reproduction studies of mesalamine in rats and rabbits at oral doses approximately 1.9 times (rat) and 3.9 times (rabbit) the recommended human dose. Mesalamine should be used during pregnancy only if clearly needed.

Human Data

Mesalamine crosses the placenta. In prospective and retrospective studies of over 600 women exposed to mesalamine during pregnancy, the observed rate of congenital malformations was not increased above the background rate in the general population. Some data show an increased rate of preterm birth, stillbirth, and low birth weight, but it is unclear whether this was due to underlying maternal disease, drug exposure, or both, as active inflammatory bowel disease is also associated with adverse pregnancy outcomes.

Animal data

Reproduction studies with mesalamine were performed during organogenesis in rats and rabbits at oral doses up to 480 mg/kg/day. There was no evidence of impaired fertility or harm to the fetus. These mesalamine doses were about 1.9 times (rat) and 3.9 times (rabbit) the recommended human dose, based on body surface area.

8.2 Lactation

Mesalamine and its N-acetyl metabolite are present in human milk. In published lactation studies, maternal mesalamine doses from various oral and rectal formulations and products ranged from 500 mg to 3 g daily. The concentration of mesalamine in milk ranged from non-detectable to 0.11 mg/L. The concentration of the N-acetyl-5-aminosalicylic acid metabolite ranged from 5 mg/L to 18.1 mg/L. Based on these concentrations, estimated infant daily doses for an exclusively breastfed infant are 0 mg/kg/day to 0.017 mg/kg/day of mesalamine and 0.75 mg/kg/day to 2.72 mg/kg/day of N-acetyl-5-aminosalicylic acid. The developmental and health benefits of breastfeeding should be considered along with the mother’s clinical need for mesalamine and any potential adverse effects on the breastfed child from the drug or from the underlying maternal condition. Caution should be exercised when mesalamine delayed-release capsules are administered to a nursing woman.

8.4 Pediatric Use

The safety and effectiveness of mesalamine delayed-release capsules for the treatment of mildly to moderately active ulcerative colitis in pediatric patients 5 to 17 years of age has been established based on adequate and well-controlled studies using mesalamine delayed-release 400 mg tablets. Use of mesalamine delayed-release capsules in these pediatric age groups is supported by evidence from adequate and well controlled studies of mesalamine delayed-release 400 mg tablets in adults and a single 6-week study in 82 pediatric patients 5 to 17 years of age [see Adverse Reactions (6.1), Clinical Pharmacology (12.3), Clinical Studies (14.1)].

The safety and effectiveness of mesalamine delayed-release capsules for the treatment of mildly to moderately active ulcerative colitis in pediatric patients below the age of 5 years have not been established. The safety and effectiveness of mesalamine delayed-release capsules in the maintenance of remission of ulcerative colitis in pediatric patients have not been established.

8.5 Geriatric Use

Clinical studies of mesalamine delayed-release tablets did not include sufficient numbers of patients aged 65 years and over to determine whether they respond differently than younger patients. Reports from uncontrolled clinical studies and postmarketing experience suggest a higher incidence of blood dyscrasias (agranulocytosis, neutropenia, pancytopenia) in subjects receiving mesalamine delayed-release tablets who are 65 years or older compared to younger patients taking mesalamine-containing products such as mesalamine delayed-release capsules. Monitor complete blood cell counts and platelet counts in elderly patients during treatment with mesalamine delayed-release capsules.

In general, consider the greater frequency of decreased hepatic, renal, or cardiac function, and of concomitant disease or other drug therapy in elderly patients when prescribing mesalamine delayed-release capsules [see Use in Specific Populations (8.6)].

8.6 Renal Impairment

Mesalamine is known to be substantially excreted by the kidney, and the risk of toxic reactions may be greater in patients with impaired renal function. Evaluate renal function in all patients prior to initiation and periodically while on mesalamine delayed-release capsules therapy. Monitor patients with known renal impairment or history of renal disease or taking nephrotoxic drugs for decreased renal function and mesalamine-related adverse reactions. Discontinue mesalamine delayed-release capsules if renal function deteriorates while on therapy [see Warnings and Precautions (5.1), Adverse Reactions (6.2), Drug Interactions (7.1)].

10 OVERDOSAGE

Mesalamine delayed-release capsules is an aminosalicylate, and symptoms of salicylate toxicity include nausea, vomiting and abdominal pain, tachypnea, hyperpnea, tinnitus, and neurologic symptoms (headache, dizziness, confusion, seizures). Severe salicylate intoxication may lead to electrolyte and blood pH imbalance and potentially to other organ (e.g., renal and liver) involvement. There is no specific antidote for mesalamine overdose; however, conventional therapy for salicylate toxicity may be beneficial in the event of acute overdosage and may include gastrointestinal tract decontamination to prevent of further absorption. Correct fluid and electrolyte imbalance by the administration of appropriate intravenous therapy and maintain adequate renal function.

Mesalamine delayed-release capsules is a pH dependent delayed-release product and this factor should be considered when treating a suspected overdose.

11 DESCRIPTION

Each Mesalamine delayed-release capsule for oral administration contains four 100 mg tablets of mesalamine, USP an aminosalicylate. Mesalamine delayed-release capsules contain acrylic based resin, methacrylic acid copolymer (Eudragit S), which dissolves at pH 7 or greater and releases mesalamine in the terminal ileum and beyond for topical anti-inflammatory action in the colon. Mesalamine, USP (also referred to as 5-aminosalicylic acid or 5-ASA) has the chemical name 5-amino-2-hydroxybenzoic acid. Its structural formula is:

C7H7NO3 M.W. 153.14

Inactive Ingredients: Each capsule contains colloidal silicon dioxide, dibutyl sebacate, hypromellose, iron oxide black, iron oxide red, lactose monohydrate, magnesium stearate, methacrylic acid copolymer, polyethylene glycol, potassium hydroxide, povidone, propylene glycol, shellac, sodium starch glycolate (potato), strong ammonia solution and talc.

12 CLINICAL PHARMACOLOGY

12.1 Mechanism of Action

The mechanism of action of mesalamine is not fully understood, but appears to be a topical anti-inflammatory effect on colonic epithelial cells. Mucosal production of arachidonic acid metabolites, both through the cyclooxygenase pathways, that is, prostanoids, and through the lipoxygenase pathways, that is, leukotrienes and hydroxyeicosatetraenoic acids, is increased in patients with ulcerative colitis, and it is possible that mesalamine diminishes inflammation by blocking cyclooxygenase and inhibiting prostaglandin production in the colon.

12.3 Pharmacokinetics

Absorption

Approximately 28% of mesalamine in mesalamine delayed-release formulation is absorbed after oral ingestion. Following replicate single dose oral administration of mesalamine delayed-release 400 mg capsules containing four 100 mg tablets in healthy subjects (N = 146) under fasted conditions, the mean Cmax, AUC8-48 and AUCtldc values were 150 ± 235 ng/mL, 640 ± 521 ng.h/mL, and 909 ± 777 ng.h/mL, respectively. The median [range] Tmax for mesalamine following mesalamine delayed-release 400 mg capsules containing four 100 mg tablets was approximately 10 hours [5.5 to 48 hours], reflecting the delayed-release characteristics of the formulation.

A high fat meal increased systemic exposure of mesalamine (geometric mean Cmax: ↑ 32%; AUC8-48 h: ↑ 46%; AUC: ↑ 29%) and delayed the median tmax by approximately 4 hours compared to results in the fasted state. The observed differences in mesalamine exposure due to concomitant food intake are not considered to be clinically relevant at the total daily dosage of 2.4 grams per day.

Elimination

Metabolism

The absorbed mesalamine is rapidly acetylated in the gut mucosal wall and by the liver to N-acetyl-5-aminosalicylic acid.

Excretion

Absorbed mesalamine is excreted mainly by the kidney as N-acetyl-5-aminosalicylic acid. Unabsorbed mesalamine is excreted in feces.

After intravenous administration, the elimination half-life of mesalamine is reported to be approximately 40 minutes. After oral dosing, the median terminal t1/2 values for mesalamine are usually about 25 hours, but are variable, ranging from 1.5 to 296 hours. There is a large inter-subject and intra-subject variability in the plasma concentrations of mesalamine and N-acetyl-5-aminosalicylic acid and in their terminal half-lives following administration of mesalamine.

Specific Populations

Pediatric Patients

In a dose-ranging pharmacokinetic study evaluating 30 mg/kg, 60 mg/kg and 90 mg/kg per day doses of mesalamine delayed-release 400 mg tablets administered twice daily for four weeks, the mean Cavg values of mesalamine in pediatric ulcerative colitis patients ranged from approximately 400 ng/mL to 2100 ng/mL based on data from all dose levels.

In a study evaluating mesalamine delayed-release tablets in pediatric ulcerative colitis patients (Study 3), mean plasma concentrations of mesalamine (based on sparse sampling) were 820 to 988 ng/mL at the low dose level (that is, 1.2, 2 or 2.4 grams/day based on body weight strata of 17 to less than 33 kg, 33 to less than 54 kg, and 54 to 90 kg, respectively).

13 NONCLINICAL TOXICOLOGY

13.1 Carcinogenesis, Mutagenesis, Impairment of Fertility

Carcinogenesis

Mesalamine was not carcinogenic at dietary doses of up to 480 mg/kg/day in rats and 2000 mg/kg/day in mice, which are about 2.9 and 6.1 times the maximum recommended maintenance dose of mesalamine of 1.6 grams per day or 26.7 mg/kg/day, based on 60 kg body weight, respectively, based on body surface area.

Mutagenesis

Mesalamine was negative in the Ames assay for mutagenesis, negative for induction of sister chromatid exchanges (SCE) and chromosomal aberrations in Chinese hamster ovary cells in vitro, and negative for induction of micronuclei (MN) in mouse bone marrow polychromatic erythrocytes.

Impairment of Fertility

Mesalamine, at oral doses up to 480 mg/kg/day (about 1.9 times the recommended human treatment dose on a body surface area basis), was found to have no effect on fertility or reproductive performance of male and female rats.

13.2 Animal Toxicology and/or Pharmacology

In animal studies (rats, mice, dogs), the kidney was the principal organ for toxicity. (In the following, comparisons of animal dosing to recommended human dosing are based on body surface area and a 2.4 grams per day dose for a 60 kg person.)

Mesalamine causes renal papillary necrosis in rats at single doses of approximately 750 mg/kg to 1000 mg/kg (approximately 3 to 4 times the recommended human dose based on body surface area). Doses of 170 and 360 mg/kg/day (about 0.7 and 1.5 times the recommended human dose based on body surface area) given to rats for six months produced papillary necrosis, papillary edema, tubular degeneration, tubular mineralization, and urothelial hyperplasia.

In mice, oral doses of 4000 mg/kg/day mesalamine (approximately 8 times the recommended human dose based on body surface area) for three months produced tubular nephrosis, multifocal/diffuse tubulo-interstitial inflammation, and multifocal/diffuse papillary necrosis.

In dogs, single doses of 6000 mg (approximately 8 times the recommended human dose based on body surface area) of delayed-release mesalamine tablets resulted in renal papillary necrosis but were not fatal. Renal changes have occurred in dogs given chronic administration of mesalamine at doses of 80 mg/kg/day (1.1 times the recommended human dose based on body surface area).

14 CLINICAL STUDIES

The safety and efficacy of mesalamine has been established based on adequate and well-controlled studies of mesalamine delayed-release tablets. Below is a description of the results of the adequate and well-controlled studies of mesalamine delayed-release tablets for the treatment of mildly to moderately active ulcerative colitis in adults and pediatric patients 5 to 17 years of age and the maintenance of remission of ulcerative colitis in adults.

14.1 Treatment of Mildly to Moderately Active Ulcerative Colitis

Adults

Two placebo-controlled studies (Studies 1 and 2) have demonstrated the efficacy of mesalamine delayed-release tablets in patients with mildly to moderately active ulcerative colitis.

In one randomized, double-blind, multi-center, placebo-controlled clinical trial of 6 weeks’ duration in 158 patients (Study 1), patients received mesalamine delayed release dosages of 1.6 grams per day (800 mg twice a day; n=53) and 2.4 grams per day (800 mg three times a day; n=53), compared to placebo (n=52). The scoring system for determination of treatment efficacy included assessment of stool frequency, rectal bleeding, sigmoidoscopic findings, patient’s functional assessment, and physician global assessment. At the dosage of 2.4 grams per day, 21 of 43 (49%) patients using mesalamine delayed release tablets showed an improvement in sigmoidoscopic appearance of the bowel compared to 12 of 44 (27%) patients using placebo (p = 0.048). In addition, significantly more patients in the mesalamine delayed release tablets 2.4 grams per day group showed improvement in rectal bleeding and stool frequency. The 1.6 grams per day dosage regimen is not recommended because it did not produce consistent evidence of effectiveness [see Dosage and Administration (2.2)].

In a second randomized, double-blind, placebo-controlled clinical trial of 6 weeks’ duration in 87 patients (Study 2), patients received mesalamine delayed release tablets of 1.6 grams per day (400 mg four times a day; n=11) and 4.8 grams per day (1.2 grams four times a day; n=38), compared to placebo four times a day (n=38). Mesalamine delayed release tablets 4.8 grams per day for 6 weeks resulted in sigmoidoscopic improvement in 28 of 38 (74%) patients compared to 10 of 38 (26%) placebo patients (p less than 0.001). Also, more patients in the mesalamine delayed release tablets 4.8 grams per day group than the placebo group showed improvement in overall symptoms. The 4.8 grams per day dosage regimen is not recommended because greater efficacy was not demonstrated with this dosage compared to the 2.4 grams per day dosage [see Dosage and Administration (2.2)].

Pediatrics

The safety and effectiveness of mesalamine delayed release in pediatric patients 5 to 17 years of age for treatment of mildly to moderately active ulcerative colitis are supported by evidence from adequate and well controlled studies of mesalamine delayed release in adults and a single study in pediatric patients.

A randomized, double-blind, 6-week study of two dosage levels of mesalamine delayed release tablets (Study 3) was conducted in 82 pediatric patients 5 to 17 years of age with mildly or moderately active ulcerative colitis defined as a score of 10 to 55 on the Pediatric Ulcerative Colitis Activity Index (PUCAI) (which includes assessment of abdominal pain, rectal bleeding, stool consistency, number of stools per 24 hours, presence of nocturnal bowel movement and activity level, and has a total maximum score of 85; each of the subscales are scored from 0 to 10 except rectal bleeding which is scored from 0 to 30, and number of stools per 24 hours which is scored from 0 to 15) and rectal bleeding and stool frequency Mayo subscale scores of ≥1 (each of these subscales are scored from zero (normal) to three (most severe).

All patients were divided by weight category (17 to less than 33 kg, 33 to less than 54 kg, and 54 to 90 kg) and randomly assigned to receive a low dosage (1.2, 2, and 2.4 grams per day for the respective weight category) or a high dosage (2, 3.6, and 4.8 grams per day). Doses were administered every 12 hours.

The proportion of patients who achieved success based on the Truncated Mayo Score (TM-Mayo) (based on the stool frequency and rectal bleeding subscores of the Mayo Score) and based on the PUCAI was measured after 6 weeks of treatment. Success based on TM-Mayo was defined as either partial response (improvement from baseline in stool frequency or rectal bleeding subscores with no worsening in the other) or complete response (both stool frequency and rectal bleeding subscores equal 0). Success based on PUCAI was defined as either partial response (PUCAI reduction of greater than or equal to 20 points from Baseline to Week 6 with Week 6 score greater than or equal to 10) or complete response (PUCAI less than 10 at Week 6).

There were 41 patients in the low dosage group and 41 patients in the high dosage group who received at least one dose of mesalamine delayed-release 400 mg tablets; 36 patients in each dosage group completed the study. Patients were considered treatment failures if they did not achieve success or dropped out due to adverse reaction or lack of efficacy.

At Week 6, 73% of the patients in the low dosage group, and 70% of the patients in the high dosage group achieved success based on the TM-Mayo; 34% of the patients in the low dosage group and 43% of the patients in the high dosage group achieved complete response. At Week 6, 56% of the patients in the low dosage group, and 55% of the patients in the high dosage group achieved success based on the PUCAI; 46% of the patients in the low dosage group and 43% of the patients in the high dosage group achieved complete response.

The high dosage regimen is not recommended because it was not more effective than the low dosage regimen [see Dosage and Administration (2.2)].

14.2 Maintenance of Remission of Ulcerative Colitis

Adults

In a randomized, double-blind, multi-center, placebo-controlled clinical trial of 6 months’ duration in 264 patients (Study 4), patients received mesalamine delayed-release tablets of 0.8 grams per day (400 mg twice a day; n = 90) and 1.6 grams per day (400 mg four times a day; n = 87), compared to placebo four times a day (n = 87). The proportion of patients treated with 0.8 grams per day who maintained endoscopic remission was not statistically significant compared to placebo; the 0.8 grams per day dosage regimen is not recommended [see Dosage and Administration (2.3)]. The number of patients using mesalamine delayed-release tablets 1.6 grams per day who maintained endoscopic remission of ulcerative colitis was 61 of 87 (70%) compared with 42 of 87 (48%) of placebo patients (p = 0.005).

A pooled efficacy analysis of 4 maintenance trials compared mesalamine delayed release tablets at dosages of 0.8 to 2.8 grams per day, in divided doses ranging from twice daily to four times per day, with sulfasalazine, at dosages of 2 to 4 grams per day. Treatment success was seen in 59 of 98 (59%) patients using mesalamine delayed release tablets and 70 of 102 (69%) patients using sulfasalazine, a non-significant difference.

16 HOW SUPPLIED/STORAGE AND HANDLING

Mesalamine delayed-release capsules are available as clear capsules imprinted with “TEVA” and “5907” on both the cap and the body in black ink. Each capsule contains four reddish-brown, film-coated round 100 mg mesalamine tablets.

NDC 0093-5907-86 Bottle of 180 capsules

Store at 20º to 25ºC (68º to 77ºF) [see USP Controlled Room Temperature].

17 PATIENT COUNSELING INFORMATION

Administration

- Inform patients that if they are switching from a previous oral mesalamine therapy to mesalamine delayed-release capsules to discontinue their previous oral mesalamine therapy and follow the dosing instructions for mesalamine delayed-release capsules. Inform patients that two mesalamine delayed-release 400 mg capsules cannot be substituted for one mesalamine delayed-release 800 mg tablet.
- Inform patients that mesalamine delayed-release capsules can be taken with or without food.
- Instruct patients to swallow the mesalamine delayed-release capsules whole. Do not cut, break, crush or chew the capsules.
- For patients who are unable to swallow the capsules whole, carefully open the capsules and swallow the contents (four 100 mg tablets).
  - Open the number of capsules required to make up a complete dose.
  - There are 4 tablets per capsule. Ensure all tablets per capsule are swallowed and no tablets are retained in the mouth.
  - Swallow the tablets whole; do not cut, break, crush or chew the tablets.
- Drink an adequate amount of fluids.
- Inform patients that intact, partially intact, and/or tablet shells have been reported in the stool. Instruct patients to contact their healthcare provider if this occurs repeatedly.
- Inform patients that urine may become discolored reddish-brown while taking mesalamine delayed-release capsules when it comes in contact with surfaces or water treated with hypochlorite-containing bleach. If discolored urine is observed, advise patients to observe their urine flow. Report to the healthcare provider only if urine is discolored on leaving the body, before contact with any surface or water (e.g., in the toilet).
- Instruct patients to protect mesalamine delayed-release capsules from moisture. Instruct patients to close the container tightly and to leave any desiccant pouches present in the bottle along with the capsules.

Renal Impairment

- Inform patients that mesalamine delayed-release capsules may decrease their renal function, especially if they have known renal impairment or are taking nephrotoxic drugs, including NSAIDs, and periodic monitoring of renal function will be performed while they are on therapy. Advise patients to complete all blood tests ordered by their healthcare provider [see Warnings and Precautions (5.1), Drug Interactions (7.1)].

Mesalamine-Induced Acute Intolerance Syndrome and Other Hypersensitivity Reactions

- Inform patients of the signs and symptoms of hypersensitivity reactions. Instruct patients to stop taking mesalamine delayed-release capsules and report to their healthcare provider if they experience new or worsening symptoms of Acute Intolerance Syndrome (cramping, abdominal pain, bloody diarrhea, fever, headache, malaise, conjunctivitis and rash) or other symptoms suggestive of mesalamine-induced hypersensitivity [see Warnings and Precautions (5.2, 5.3)].

Hepatic Failure

- Inform patients with known liver disease of the signs and symptoms of worsening liver function and advise them to report to their healthcare provider if they experience such signs or symptoms [see Warnings and Precautions (5.4)].

Severe Cutaneous Adverse Reactions

- Inform patients of the signs and symptoms of severe cutaneous adverse reactions. Instruct patients to stop taking mesalamine delayed-release capsules and report to their healthcare provider at first appearance of a severe cutaneous adverse reaction or other sign of hypersensitivity [see Warnings and Precautions (5.5)].

Photosensitivity

- Advise patients with pre-existing skin conditions to avoid sun exposure, wear protective clothing, and use a broad-spectrum sunscreen when outdoors [see Warnings and Precautions (5.6)].

Nephrolithiasis

- Instruct patients to maintain an adequate fluid intake during treatment in order to minimize the risk of kidney stone formation and to contact their healthcare provider if they experience signs or symptoms of a kidney stone (e.g., severe side or back pain, blood in the urine) [see Warnings and Precautions (5.7)].

Iron Content of Mesalamine Delayed-Release Capsules

- Advise patients to inform their healthcare provider if they take iron-containing supplements [see Warnings and Precaution (5.8)].

Blood Disorders

- Inform elderly patients and those taking azathioprine or 6-mercaptopurine of the risk for blood disorders and the need for periodic monitoring of complete blood cell counts and platelet counts while on therapy. Advise patients to complete all blood tests ordered by their healthcare provider [see Drug Interactions (7.2), Use in Specific Populations (8.5)].

Manufactured In Israel By:
Teva Pharmaceutical Ind. Ltd.
Kfar Saba, 4410202, Israel

Manufactured For:
Teva Pharmaceuticals
Parsippany, NJ 07054

Rev. H 5/2025

PACKAGE LABEL.PRINCIPAL DISPLAY PANEL

NDC 0093-5907-86

Mesalamine Delayed-Release Capsules

400 mg

Swallow the capsule or tablets whole; do not cut, break, crush or chew the capsule or tablets. The capsule may be carefully opened and the contents (tablets) can be swallowed.

Not Bioequivalent to Asacol® HD*

Rx only

180 CAPSULES